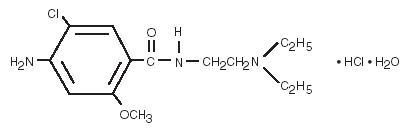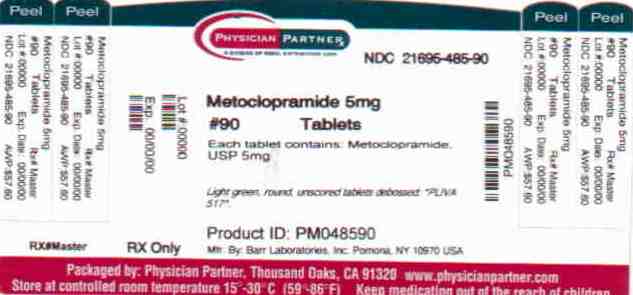 DRUG LABEL: Metoclopramide
NDC: 21695-485 | Form: TABLET
Manufacturer: Rebel Distributors Corp.
Category: prescription | Type: HUMAN PRESCRIPTION DRUG LABEL
Date: 20101004

ACTIVE INGREDIENTS: METOCLOPRAMIDE HYDROCHLORIDE 5 mg/1 1
INACTIVE INGREDIENTS: ANHYDROUS LACTOSE; MAGNESIUM STEARATE; POVIDONE; STARCH, CORN; SODIUM STARCH GLYCOLATE TYPE A POTATO; D&C YELLOW NO. 10; FD&C BLUE NO. 1

METOCLOPRAMIDE
TABLETS, USP

DESCRIPTION

Metoclopramide hydrochloride is a white or practically white, crystalline, odorless or practically odorless powder. It is very soluble in water, freely soluble in alcohol, sparingly soluble in chloroform, practically insoluble in ether. Chemically, it is 4-amino-5-chloro- N-[2-(diethylamino) ethyl]-2-methoxybenzamide monohydrochloride monohydrate. Its structural formula is as follows:

C14H22CIN3O2•HCl•H2O Molecular Weight: 354.3

Each tablet for oral administration contains metoclopramide hydrochloride, equivalent to either 5 mg or 10 mg metoclopramide. Tablets also contain as inactive ingredients anhydrous lactose, magnesium stearate, povidone, pregelatinized starch, sodium starch glycolate and (5 mg only) D&C Yellow #10 and FD&C Blue #1.

CLINICAL PHARMACOLOGY

Metoclopramide stimulates motility of the upper gastrointestinal tract without stimulating gastric, biliary, or pancreatic secretions. Its mode of action is unclear. It seems to sensitize tissues to the action of acetylcholine. The effect of metoclopramide on motility is not dependent on intact vagal innervation, but it can be abolished by anticholinergic drugs.

Metoclopramide increases the tone and amplitude of gastric (especially antral) contractions, relaxes the pyloric sphincter and the duodenal bulb, and increases peristalsis of the duodenum and jejunum resulting in accelerated gastric emptying and intestinal transit. It increases the resting tone of the lower esophageal sphincter. It has little, if any, effect on the motility of the colon or gallbladder.

In patients with gastroesophageal reflux and low LESP (lower esophageal sphincter pressure), single oral doses of metoclopramide produce dose-related increases in LESP. Effects begin at about 5 mg and increase through 20 mg (the largest dose tested). The increase in LESP from a 5 mg dose lasts about 45 minutes and that of 20 mg lasts between 2 and 3 hours. Increased rate of stomach emptying has been observed with single oral doses of 10 mg.

The antiemetic properties of metoclopramide appear to be a result of its antagonism of central and peripheral dopamine receptors. Dopamine produces nausea and vomiting by stimulation of the medullary chemoreceptor trigger zone (CTZ), and metoclopramide blocks stimulation of the CTZ by agents like l-dopa or apomorphine which are known to increase dopamine levels or to possess dopamine-like effects. Metoclopramide also abolishes the slowing of gastric emptying caused by apomorphine.

Like the phenothiazines and related drugs, which are also dopamine antagonists, metoclopramide produces sedation and may produce extrapyramidal reactions, although these are comparatively rare (see WARNINGS). Metoclopramide inhibits the central and peripheral effects of apomorphine, induces release of prolactin and causes a transient increase in circulating aldosterone levels, which may be associated with transient fluid retention.

The onset of pharmacological action of metoclopramide is 1 to 3 minutes following an intravenous dose, 10 to 15 minutes following intramuscular administration, and 30 to 60 minutes following an oral dose; pharmacological effects persist for 1 to 2 hours.

Pharmacokinetics:

Metoclopramide is rapidly and well absorbed. Relative to an intravenous dose of 20 mg, the absolute oral bioavailability of metoclopramide is 80% ± 15.5% as demonstrated in a crossover study of 18 subjects. Peak plasma concentrations occur at about 1 to 2 hours after a single oral dose. Similar time to peak is observed after individual doses at steady state.

In a single dose study of 12 subjects, the area under the drug concentration-time curve increased linearly with doses from 20 to 100 mg. Peak concentrations increase linearly with dose; time to peak concentrations remains the same; whole body clearance is unchanged; and the elimination rate remains the same. The average elimination halflife in individuals with normal renal function is 5 to 6 hours. Linear kinetic processes adequately describe the absorption and elimination of metoclopramide.

Approximately 85% of the radioactivity of an orally administered dose appears in the urine within 72 hours. Of the 85% eliminated in the urine, about half is present as free or conjugated metoclopramide.

The drug is not extensively bound to plasma proteins (about 30%). The whole body volume of distribution is high (about 3.5 L/kg) which suggests extensive distribution of drug to the tissues.

Renal impairment affects the clearance of metoclopramide. In a study with patients with varying degrees of renal impairment, a reduction in creatinine clearance was correlated with a reduction in plasma clearance, renal clearance, non-renal clearance, and increase in elimination half-life. The kinetics of metoclopramide in the presence of renal impairment remained linear however. The reduction in clearance as a result of renal impairment suggests that adjustment downward of maintenance dosage should be done to avoid drug accumulation.

Adult Pharmacokinetic Data
Parameter | Value
Vd (L/kg) | ~ 3.5
Plasma Protein Binding | ~ 30%
t1/2 (hr) | 5-6
Oral Bioavailability | 80% ± 15.5%

In pediatric patients, the pharmacodynamics of metoclopramide following oral and intravenous administration are highly variable and a concentration-effect relationship has not been established.

There are insufficient reliable data to conclude whether the pharmacokinetics of metoclopramide in adults and the pediatric population are similar. Although there are insufficient data to support the efficacy of metoclopramide in pediatric patients with symptomatic gastroesophageal reflux (GER) its pharmacokinetics have been studied in these patient populations.

In an open-label study, six pediatric patients (age range, 3.5 weeks to 5.4 months) with GER received metoclopramide 0.15 mg/kg oral solution every 6 hours for 10 doses. The mean peak plasma concentration of metoclopramide after the tenth dose was 2-fold (56.8 mcg/L) higher compared to that observed after the first dose (29 mcg/L) indicating drug accumulation with repeated dosing. After the tenth dose, the mean time to reach peak concentrations (2.2 hr), half-life (4.1 hr), clearance (0.67 L/h/kg), and volume of distribution (4.4 L/kg) of metoclopramide were similar to those observed after the first dose. In the youngest patient (age, 3.5 weeks), metoclopramide half-life after the first and the tenth dose (23.1 and 10.3 hr, respectively) was significantly longer compared to other infants due to reduced clearance. This may be attributed to immature hepatic and renal systems at birth.

Pediatric Pharmacokinetic Study
Reference | Dose, Route | t 1/2 (hr) | Cl (L/hr/kg) | Vd (L/kg) | Cmax (mcg/L)
1. | 0.15 mg/kg oral soln, multiple dose | 4.1 a,b | 0.67±0.14 | 4.4±0.65 (Vd area) | 1st dose = 29±2.3 10th dose = 56.8 ± 10.5
a. Data presented as means ± SEM.
b. SEM not available.
1. Kearns, GL, et al. J Pediatric Gastroenterol Nutr 7(6):823-829, 1988.

INDICATIONS AND USAGE

Symptomatic Gastroesophageal Reflux: Metoclopramide tablets are indicated as short-term (4 to 12 weeks) therapy for adults with symptomatic, documented gastroesophageal reflux who fail to respond to conventional therapy.

The principal effect of metoclopramide is on symptoms of postprandial and daytime heartburn with less observed effect on nocturnal symptoms. If symptoms are confined to particular situations, such as following the evening meal, use of metoclopramide as single doses prior to the provocative situation should be considered, rather than using the drug throughout the day. Healing of esophageal ulcers and erosions has been endoscopically demonstrated at the end of a 12-week trial using doses of 15 mg q.i.d. As there is no documented correlation between symptoms and healing of esophageal lesions, patients with documented lesions should be monitored endoscopically.

Diabetic Gastroparesis (Diabetic Gastric Stasis): Metoclopramide is indicated for the relief of symptoms associated with acute and recurrent diabetic gastric stasis. The usual manifestations of delayed gastric emptying (e.g., nausea, vomiting, heartburn, persistent fullness after meals, and anorexia) appear to respond to metoclopramide within different time intervals. Significant relief of nausea occurs early and continues to improve over a three week period. Relief of vomiting and anorexia may precede the relief of abdominal fullness by one week or more.

CONTRAINDICATIONS

Metoclopramide should not be used whenever stimulation of gastrointestinal motility might be dangerous, e.g., in the presence of gastrointestinal hemorrhage, mechanical obstruction, or perforation.

Metoclopramide is contraindicated in patients with pheochromocytoma because the drug may cause a hypertensive crisis, probably due to release of catecholamines from the tumor. Such hypertensive crises may be controlled by phentolamine.

Metoclopramide is contraindicated in patients with known sensitivity or intolerance to the drug.

Metoclopramide should not be used in epileptics or patients receiving other drugs which are likely to cause extrapyramidal reactions, since the frequency and severity of seizures or extrapyramidal reactions may be increased.

WARNINGS

Mental depression has occurred in patients with and without prior history of depression. Symptoms have ranged from mild to severe and have included suicidal ideation and suicide. Metoclopramide should be given to patients with a prior history of depression only if the expected benefits outweigh the potential risks.

Extrapyramidal symptoms, manifested primarily as acute dystonic reactions, occur in approximately 1 in 500 patients treated with the usual adult dosages of 30 to 40 mg/day of metoclopramide. These usually are seen during the first 24 to 48 hours of treatment with metoclopramide, occur more frequently in pediatric patients and adult patients less than 30 years of age and are even more frequent at the higher doses. These symptoms may include involuntary movements of limbs and facial grimacing, torticollis, oculogyric crisis, rhythmic protrusion of tongue, bulbar type of speech, trismus, or dystonic reactions resembling tetanus. Rarely, dystonic reactions may present as stridor and dyspnea, possibly due to laryngo-spasm. If these symptoms should occur, inject 50 mg of Benadryl® (diphenhydramine hydrochloride) intramuscularly, and they usually will subside. Cogentin® (benztropine mesylate), 1 to 2 mg intramuscularly, may also be used to reverse these reactions.

Parkinsonian-like symptoms have occurred, more commonly within the first 6 months after beginning treatment with metoclopramide, but occasionally after longer periods. These symptoms generally subside within 2 to 3 months following discontinuance of metoclopramide. Patients with preexisting Parkinson’s disease should be given metoclopramide cautiously, if at all, since such patients may experience exacerbation of parkinsonian symptoms when taking metoclopramide.

Tardive Dyskinesia: Tardive dyskinesia, a syndrome consisting of potentially irreversible, involuntary, dyskinetic movements may develop in patients treated with metoclopramide. Although the prevalence of the syndrome appears to be highest among the elderly, especially elderly women, it is impossible to predict which patients are likely to develop the syndrome.

Both the risk of developing the syndrome and the likelihood that it will become irreversible are believed to increase with the duration of treatment and the total cumulative dose.

Less commonly, the syndrome can develop after relatively brief treatment periods at low doses; in these cases, symptoms appear more likely to be reversible.

There is no known treatment for established cases of tardive dyskinesia although the syndrome may remit, partially or completely, within several weeks-to-months after metoclopramide is withdrawn. Metoclopramide itself, however, may suppress (or partially suppress) the signs of tardive dyskinesia, thereby masking the underlying disease process. The effect of this symptomatic suppression upon the long-term course of the syndrome is unknown. Therefore, the use of metoclopramide for the symptomatic control of tardive dyskinesia is not recommended.

PRECAUTIONS

General:

In one study in hypertensive patients, intravenously administered metoclopramide was shown to release catecholamines; hence, caution should be exercised when metoclopramide is used in patients with hypertension.

Because metoclopramide produces a transient increase in plasma aldosterone, certain patients, especially those with cirrhosis or congestive heart failure, may be at risk of developing fluid retention and volume overload. If these side effects occur at any time during metoclopramide therapy, the drug should be discontinued.

Giving a promotility drug such as metoclopramide theoretically could put increased pressure on suture lines following a gut anastomosis or closure. This possibility should be considered and weighed when deciding whether to use metoclopramide or nasogastric suction in the prevention of postoperative nausea and vomiting.

Information for Patients:

Metoclopramide may impair the mental and/or physical abilities required for the performance of hazardous tasks such as operating machinery or driving a motor vehicle. The ambulatory patient should be cautioned accordingly.

Drug Interactions:

The effects of metoclopramide on gastrointestinal motility are antagonized by anticholinergic drugs and narcotic analgesics. Additive sedative effects can occur when metoclopramide is given with alcohol, sedatives, hypnotics, narcotics or tranquilizers.

The finding that metoclopramide releases catecholamines in patients with essential hypertension suggests that it should be used cautiously, if at all, in patients receiving monoamine oxidase inhibitors.

Absorption of drugs from the stomach may be diminished (e.g., digoxin) by metoclopramide, whereas the rate and/or extent of absorption of drugs from the small bowel may be increased (e.g., acetaminophen, tetracycline, levodopa, ethanol, cyclosporine).

Gastroparesis (gastric stasis) may be responsible for poor diabetic control in some patients. Exogenously administered insulin may begin to act before food has left the stomach and lead to hypoglycemia. Because the action of metoclopramide will influence the delivery of food to the intestines and thus the rate of absorption, insulin dosage or timing of dosage may require adjustment.

Carcinogenesis, Mutagenesis, Impairment of Fertility:

A 77-week study was conducted in rats with oral doses up to about 40 times the maximum recommended human daily dose. Metoclopramide elevates prolactin levels and the elevation persists during chronic administration. Tissue culture experiments indicate that approximately one-third of human breast cancers are prolactin-dependent in vitro, a factor of potential importance if the prescription of metoclopramide is contemplated in a patient with previously detected breast cancer. Although disturbances, such as galactorrhea, amenorrhea, gynecomastia, and impotence have been reported with prolactin-elevating drugs, the clinical significance of elevated serum prolactin levels is unknown for most patients. An increase in mammary neoplasms has been found in rodents after chronic administration of prolactin-stimulating neuroleptic drugs and metoclopramide. Neither clinical studies nor epidemiologic studies conducted to date, however, have shown an association between chronic administration of these drugs and mammary tumorigenesis; the available evidence is too limited to be conclusive at this time.

An Ames mutagenicity test performed on metoclopramide was negative.

Pregnancy Category B:

Reproduction studies performed in rats, mice, and rabbits by the I.V., I.M., S.C., and oral routes at maximum levels ranging from 12 to 250 times the human dose have demonstrated no impairment of fertility or significant harm to the fetus due to metoclopramide. There are, however, no adequate and well-controlled studies in pregnant women. Because animal reproduction studies are not always predictive of human response, this drug should be used during pregnancy only if clearly needed.

Nursing Mothers:

Metoclopramide is excreted in human milk. Caution should be exercised when metoclopramide is administered to a nursing mother.

Pediatric Use:

Safety and effectiveness in pediatric patients have not been established except as stated to facilitate small bowel intubation (see OVERDOSAGE and DOSAGE AND ADMINISTRATION).

Care should be exercised in administering metoclopramide to neonates since prolonged clearance may produce excessive serum concentrations (see CLINICAL PHARMACOLOGY—Pharmacokinetics). In addition, neonates have reduced levels of nicotinamide adenine dinucleotide-methemoglobin reductase which, in combination with the aforementioned pharmacokinetic factors, make neonates more susceptible to methemoglobinemia (see OVERDOSAGE).

The safety profile of metoclopramide in adults cannot be extrapolated to pediatric patients. Dystonias and other extrapyramidal reactions associated with metoclopramide are more common in the pediatric population than in adults. (See WARNINGS and ADVERSE REACTIONS—Extrapyramidal Reactions.)

ADVERSE REACTIONS

In general, the incidence of adverse reactions correlates with the dose and duration of metoclopramide administration. The following reactions have been reported, although in most instances, data do not permit an estimate of frequency.

CNS Effects: Restlessness, drowsiness, fatigue, and lassitude occur in approximately 10% of patients receiving the most commonly prescribed dosage of 10 mg q.i.d. (see PRECAUTIONS). Insomnia, headache, confusion, dizziness, or mental depression with suicidal ideation (see WARNINGS) occur less frequently. There are isolated reports of convulsive seizures without clearcut relationships to metoclopramide. Rarely, hallucinations have been reported.

Extrapyramidal Reactions (EPS): Acute dystonic reactions, the most common type of EPS associated with metoclopramide, occur in approximately 0.2% of patients (1 in 500) treated with 30 to 40 mg of metoclopramide per day. Symptoms include involuntary movements of limbs, facial grimacing, torticollis, oculogyric crisis, rhythmic protrusion of tongue, bulbar type of speech, trismus, opisthotonus (tetanus-like reactions), and rarely, stridor and dyspnea possibly due to laryngospasm; ordinarily these symptoms are readily reversed by diphenhydramine (see WARNINGS).

Parkinsonian-like symptoms may include bradykinesia, tremor, cogwheel rigidity, masklike facies (see WARNINGS).

Tardive dyskinesia most frequently is characterized by involuntary movements of the tongue, face, mouth, or jaw, and sometimes by involuntary movements of the trunk and/or extremities; movements may be choreoathetotic in appearance (see WARNINGS).

Motor restlessness (akathisia) may consist of feelings of anxiety, agitation, jitteriness, and insomnia, as well as inability to sit still, pacing, foot-tapping. These symptoms may disappear spontaneously or respond to a reduction in dosage.

Endocrine Disturbances: Galactorrhea, amenorrhea, gynecomastia, impotence secondary to hyperprolactinemia (see PRECAUTIONS). Fluid retention secondary to transient elevation of aldosterone (see CLINICAL PHARMACOLOGY).

Cardiovascular: Hypotension, hypertension, supraventricular tachycardia, bradycardia, fluid retention, acute congestive heart failure and possible AV block (see CONTRAINDICATIONS and PRECAUTIONS).

Gastrointestinal: Nausea and bowel disturbances, primarily diarrhea.

Hepatic: Rarely, cases of hepatotoxicity, characterized by such findings as jaundice and altered liver function tests, when metoclopramide was administered with other drugs with known hepatotoxic potential.

Renal: Urinary frequency and incontinence.

Hematologic: A few cases of neutropenia, leukopenia, or agranulocytosis, generally without clearcut relationships to metoclopramide. Methemoglobinemia, especially with overdosage in neonates (see OVERDOSAGE).

Sulfhemoglobinemia in adults.

Allergic Reactions: A few cases of rash, urticaria, or bronchospasm, especially in patients with a history of asthma. Rarely, angioneurotic edema, including glossal or laryngeal edema.

Miscellaneous: Visual disturbances. Porphyria. Rare occurrences of neuroleptic malignant syndrome (NMS) have been reported. This potentially fatal syndrome is comprised of the symptom complex of hyperthermia, altered consciousness, muscular rigidity, and autonomic dysfunction.

Transient flushing of the face and upper body, without alterations in vital signs, following high doses intravenously.

OVERDOSAGE

Symptoms of overdosage may include drowsiness, disorientation and extrapyramidal reactions. Anticholinergic or antiparkinson drugs or antihistamines with anticholinergic properties may be helpful in controlling the extrapyramidal reactions. Symptoms are self-limiting and usually disappear within 24 hours.

Hemodialysis removes relatively little metoclopramide, probably because of the small amount of the drug in blood relative to tissues. Similarly, continuous ambulatory peritoneal dialysis does not remove significant amounts of drug. It is unlikely that dosage would need to be adjusted to compensate for losses through dialysis. Dialysis is not likely to be an effective method of drug removal in overdose situations.

Unintentional overdose due to misadministration has been reported in infants and children with the use of metoclopramide oral solution. While there was no consistent pattern to the reports associated with these overdoses, events included seizures, extrapyramidal reactions, and lethargy.

Methemoglobinemia has occurred in premature and full-term neonates who were given overdoses of metoclopramide (1 to 4 mg/kg/day orally, intramuscularly or intravenously for 1 to 3 or more days).

Methemoglobinemia has not been reported in neonates treated with 0.5 mg/kg/day in divided doses. Methemoglobinemia can be reversed by the intravenous administration of methylene blue.

DOSAGE AND ADMINISTRATION

For the Relief of Symptomatic Gastroesophageal Reflux: Administer from 10 mg to 15 mg metoclopramide orally up to q.i.d. 30 minutes before each meal and at bedtime, depending upon symptoms being treated and clinical response (see CLINICAL PHARMACOLOGY and INDICATIONS AND USAGE). If symptoms occur only intermittently or at specific times of the day, use of metoclopramide in single doses up to 20 mg prior to the provoking situation may be preferred rather than continuous treatment. Occasionally, patients (such as elderly patients) who are more sensitive to the therapeutic or adverse effects of metoclopramide will require only 5 mg per dose.

Experience with esophageal erosions and ulcerations is limited, but healing has thus far been documented in one controlled trial using q.i.d. therapy at 15 mg per dose, and this regimen should be used when lesions are present, so long as it is tolerated (see ADVERSE REACTIONS). Because of the poor correlation between symptoms and endoscopic appearance of the esophagus, therapy directed at esophageal lesions is best guided by endoscopic evaluation.

Therapy longer than 12 weeks has not been evaluated and cannot be recommended. For the Relief of Symptoms Associated with Diabetic Gastroparesis (Diabetic Gastric Stasis): Administer 10 mg of metoclopramide 30 minutes before each meal and at bedtime for two to eight weeks, depending upon response and the likelihood of continued well-being upon drug discontinuation.

The initial route of administration should be determined by the severity of the presenting symptoms. If only the earliest manifestations of diabetic gastric stasis are present, oral administration of metoclopramide may be initiated. However, if severe symptoms are present, therapy should begin with Metoclopramide Injection (I.M. or I.V.) (consult labeling of the injection prior to initiating parenteral administration).

Administration of the Metoclopramide Injection up to 10 days may be required before symptoms subside, at which time oral administration may be instituted. Since diabetic gastric stasis is frequently recurrent, metoclopramide therapy should be reinstituted at the earliest manifestation.

Use in Patients with Renal or Hepatic Impairment: Since metoclopramide is excreted principally through the kidneys, in those patients whose creatinine clearance is below 40 mL/min, therapy should be initiated at approximately one-half the recommended dosage. Depending upon clinical efficacy and safety considerations, the dosage may be increased or decreased as appropriate.

See OVERDOSAGE section for information regarding dialysis.

Metoclopramide undergoes minimal hepatic metabolism, except for simple conjugation. Its safe use has been described in patients with advanced liver disease whose renal function was normal.

HOW SUPPLIED

Metoclopramide Tablets, USP:

5 mg - Light green, round, unscored tablets in bottles of 30 and 90. Debossed: PLIVA 517

10 mg - White, round, scored tablets in bottles of 15, 20, 30, 60 and 90. Debossed: PLIVA 430

Dispense in a tight, light-resistant container as defined in the USP.

Store at 20°-25°C (68°-77°F) [See USP Controlled Room Temperature].

Manufactured by:
BARR LABORATORIES, INC.
Pomona, NY 10970 USA

Distributed by:
Watson Pharma, Inc.
Corona, CA 92880 USA

Repackaged by:

Rebel Distributors Corp

Thousand Oaks, CA 91320

PRINCIPAL DISPLAY PANEL

Package Label - 5 mg Tablets
NDC 21695-485-90
Metoclopramide
Tablets, USP
5 mg*
Rebel Distributors Corp 90 Tablets Rx only